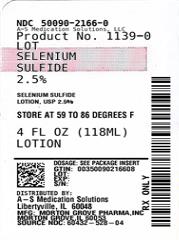 DRUG LABEL: SELENIUM SULFIDE
NDC: 50090-2166 | Form: LOTION
Manufacturer: A-S Medication Solutions
Category: prescription | Type: HUMAN PRESCRIPTION DRUG LABEL
Date: 20210226

ACTIVE INGREDIENTS: SELENIUM SULFIDE 25 mg/1 mL
INACTIVE INGREDIENTS: BENTONITE; TITANIUM DIOXIDE; WATER; ANHYDROUS CITRIC ACID; SODIUM PHOSPHATE, MONOBASIC, UNSPECIFIED FORM; SODIUM LAURYL SULFATE; DISODIUM COCOAMPHODIACETATE; GLYCOL STEARATE; LAURIC DIETHANOLAMIDE; CAPTAN; D&C YELLOW NO. 10; GLYCERYL RICINOLEATE

SELENIUM SULFIDE LOTION, USP 2.5%

SHAKE WELL BEFORE USING.

APPLICATION INSTRUCTIONS

Keep tightly capped. SHAKE WELL BEFORE USING. Product may damage jewelry; remove jewelry before use.

For treatment of tinea versicolor:

1. Apply to affected areas and lather with a small amount of water.
2. Allow to remain on skin for 10 minutes.
3. Rinse body thoroughly.
4. Repeat this procedure once a day for 7 days.

For treatment of dandruff and seborrheic dermatitis of the scalp.

1. Massage 1 or 2 teaspoonfuls of shampoo into wet scalp.
2. Allow to remain on scalp for 2 to 3 minutes.
3. Rinse scalp thoroughly.
4. Repeat application and rinse thoroughly.
5. After treatment, wash hands well.
6. Repeat treatments as directed by physician.

WARNINGS AND PRECAUTIONS

For External Use Only. Do not use on broken skin or inflamed areas. If allergic reactions occur, discontinue use. Avoid getting shampoo in eyes or in contact with genital area as it may cause irritation and burning.

FOR EXTERNAL USE ONLY. WARNING: KEEP THIS AND ALL MEDICATIONS OUT OF THE REACH OF CHILDREN.

Store at controlled room temperature, (15 - 30) °C ((59 - 86) °F) [see USP].

CLINICAL PHARMACOLOGY

Selenium sulfide appears to have a cytostatic effect on cells of the epidermis and follicular epithelium, reducing corneocyte production.

INDICATIONS AND USAGE

For treatment of tinea versicolor, seborrheic dermatitis of scalp and treatment of dandruff.

CONTRAINDICATIONS

Not to be used by patients allergic to any of its ingredients.

PRECAUTIONS

General:

Not to be used when acute inflammation or exudation is present as increased absorption may occur.

Information for Patients:

See Warnings and Precautions section under Application Instructions.

Carcinogenesis:

Dermal application of 25% and 50% solutions of 2.5% selenium sulfide lotion on mice over an 88 week period, indicated no carcinogenic effects.

Pregnancy:

WHEN USED ON BODY SURFACES FOR THE TREATMENT OF TINEA VERSICOLOR, SELENIUM SULFIDE LOTION, USP 2.5% IS CLASSIFIED AS PREGNANCY CATEGORY C. Animal reproduction studies have not been conducted with selenium sulfide. It is also not known whether selenium sulfide can cause fetal harm when applied to body surfaces of a pregnant woman or can affect reproduction capacity. Under ordinary circumstances selenium sulfide should not be used for the treatment of tinea versicolor in pregnant women.

Pediatric Use:

Safety and effectiveness in infants have not been established.

ADVERSE REACTIONS

In decreasing order of severity: skin irritation; occasional reports of increase in normal hair loss; discoloration of hair (can be avoided or minimized by thorough rinsing of hair after treatment). As with other shampoos, oiliness or dryness of hair and scalp may occur.

OVERDOSAGE

Accidental Oral Ingestion:

No documented reports of serious toxicity in humans resulting from acute ingestion of selenium sulfide, however, acute toxicity studies in animals suggest that ingestion of large amounts could result in potential human toxicity. Evacuation of the stomach contents should be considered in cases of acute oral ingestion.

DOSAGE AND ADMINISTRATION

See Application Instructions.

For treatment of tinea versicolor

Apply to affected areas and lather with a small amount of water. Allow product to remain on skin for 10 minutes, then rinse the body thoroughly. Repeat procedure once a day for 7 days.

For treatment of dandruff and seborrheic dermatitis

Usually two applications each week for two weeks will afford control. After this, the lotion may be used at less frequent intervals – weekly, every two weeks, or every 3 or 4 weeks in some cases. Should not be applied more frequently than required to maintain control.

HOW SUPPLIED

Product: 50090-2166

NDC: 50090-2166-0 118 mL in a BOTTLE, PLASTIC

WARNINGS

KEEP THIS AND ALL DRUGS OUT OF THE REACH OF CHILDREN. In case of accidental overdose, seek professional assistance or contact a Poison Control Center immediately.

Rx Only

Product No.: 8528

A50-8528-04

REV. 01-05

Manufactured By:

Morton Grove Pharmaceuticals, Inc.

Morton Grove, IL 60053